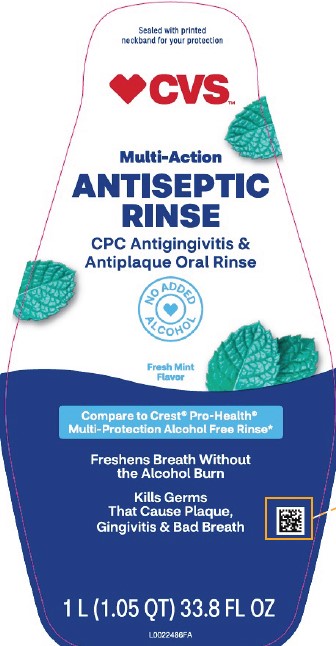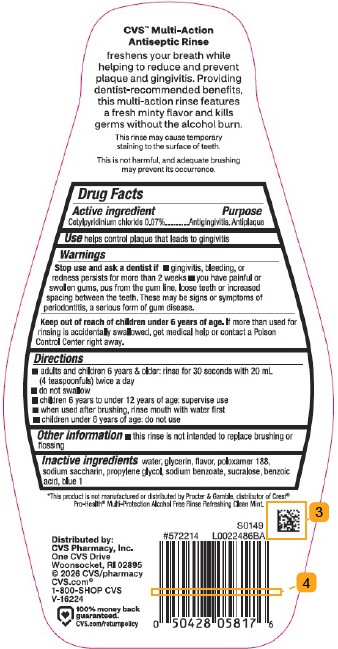 DRUG LABEL: CVS Antiseptic
NDC: 59779-299 | Form: RINSE
Manufacturer: CVS Pharmacy, Inc.
Category: otc | Type: HUMAN OTC DRUG LABEL
Date: 20260211

ACTIVE INGREDIENTS: CETYLPYRIDINIUM CHLORIDE 0.7 mg/1 mL
INACTIVE INGREDIENTS: WATER; GLYCERIN; POLOXAMER 188; SACCHARIN SODIUM; PROPYLENE GLYCOL; SODIUM BENZOATE; SUCRALOSE; BENZOIC ACID; FD&C BLUE NO. 1

CVS 299.005/299AK-AL
Multi Action Alcohol Free Antiseptic Rinse w/CPC

Claims

CVS™ Multi-Action Antiseptic Rinse

freshens your breath while helping to reduce and prevent plaque and gingivitis. Providing dentist-recommended benefits, this multi-action rinse features a fresh minty flavor and kills germs without the alcohol burn.

Disclaimers

This rinse may cause temporary staining to the surface of teeth.

This is not harmful, and adequate brushing may prevent its occurrence.

ACTIVE INGREDIENT

Cetylpyridinium chloride 0.07%

PURPOSE

Antigingivitis, Antiplaque

Use

helps control plaque that leads to gingivitis

Warnings

for this product

Stop use and ask a dentist if

- gingivitis, bleeding or redness persists for more than 2 weeks
- you have painful or swollen gums, pus from the gun line, loose teeth or increased spacing between the teeth. These may be signs or symptoms of periodontitis, a serious form of gum disease.

Keep out of reach of children under 6 years of age.

If more than used for rinsing is accidentally swallowed, get medical help or contact a Poison Control Center right away.

Directions

- adults and children 6 years + older: rinse for 30 seconds with 20 mL (4 teaspoonfuls) twice a day
- do not swallow
- children two years to under 12 years of age: supervise use
- when used after brushing, rinse mouth with water first
- children under 6 years of age: do not use

Other information

- this rinse is not intended to replace brushing or flossing

Inactive ingredients

water, glycerin, flavor, poloxamer 188, sodium saccharin, propylene glycol, sodium benzoate, sucralose, benzoic acid, blue 1

Disclaimer

*This product is not manufactured or distributed by Procter & Gamble, distributor of Crest® Pro-Health® Multi-Protection Alcohol Free Rinse Refreshing Clean Mint.

ADVERSE REACTION

Distributed by: CVS Pharmacy, Inc.

One CVS Drive, Woonsocket, RI 02895

©2026 CVS/pharmacy

CVS.com®

1-800-SHOP CVS

100% money back guaranteed.

CVS.com/returnpolicy

principal display panel

Sealed with printed neckband for your protection.

CVS™

Multi-Action ANTISEPTIC RINSE

CPC ANTIGINGIVITIS & ANTIPLAQUE ORAL RINSE

NO ADDED ALCOHOL

Fresh Mint Flavor

Compare to Crest®Pro-Health®Multi-Protection Alcohol Free Rinse*

Freshens breath without the alcohol burn

Kills germs that cause plaque, gingivitis & bad breath

1 L (1.05 QT) 33.8 FL OZ